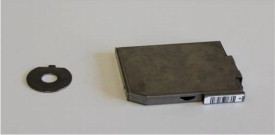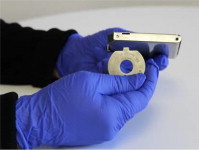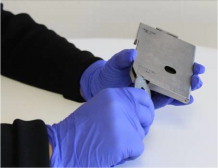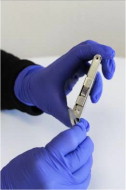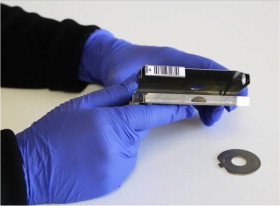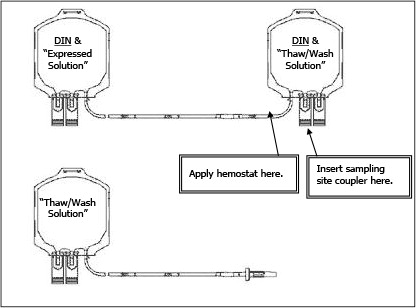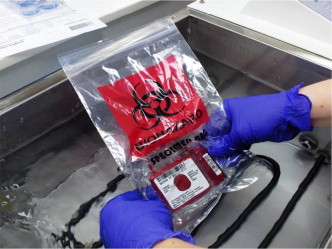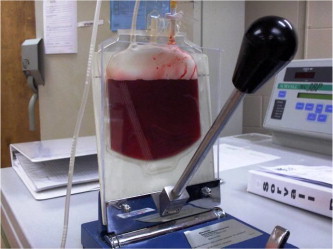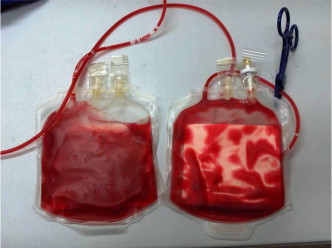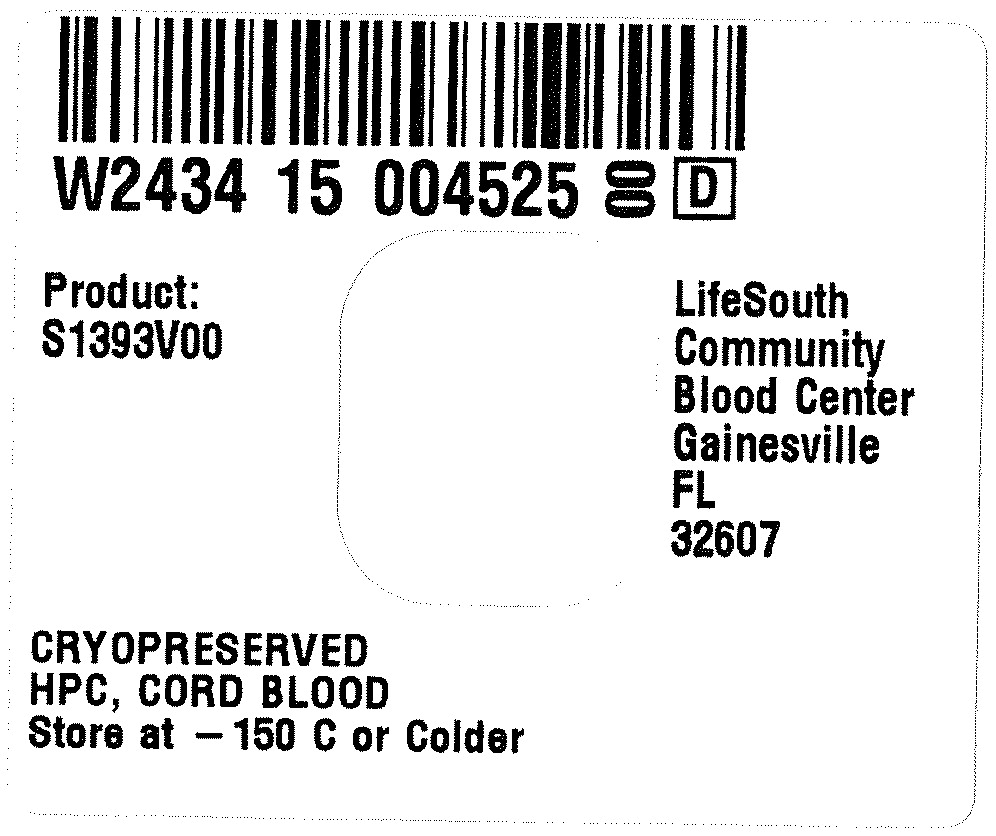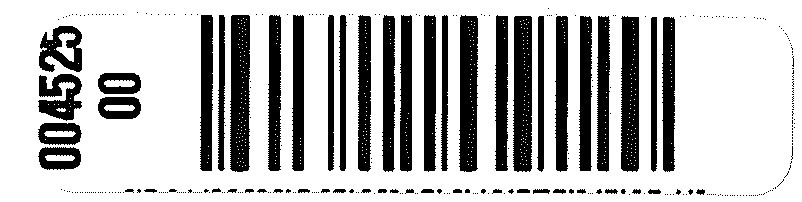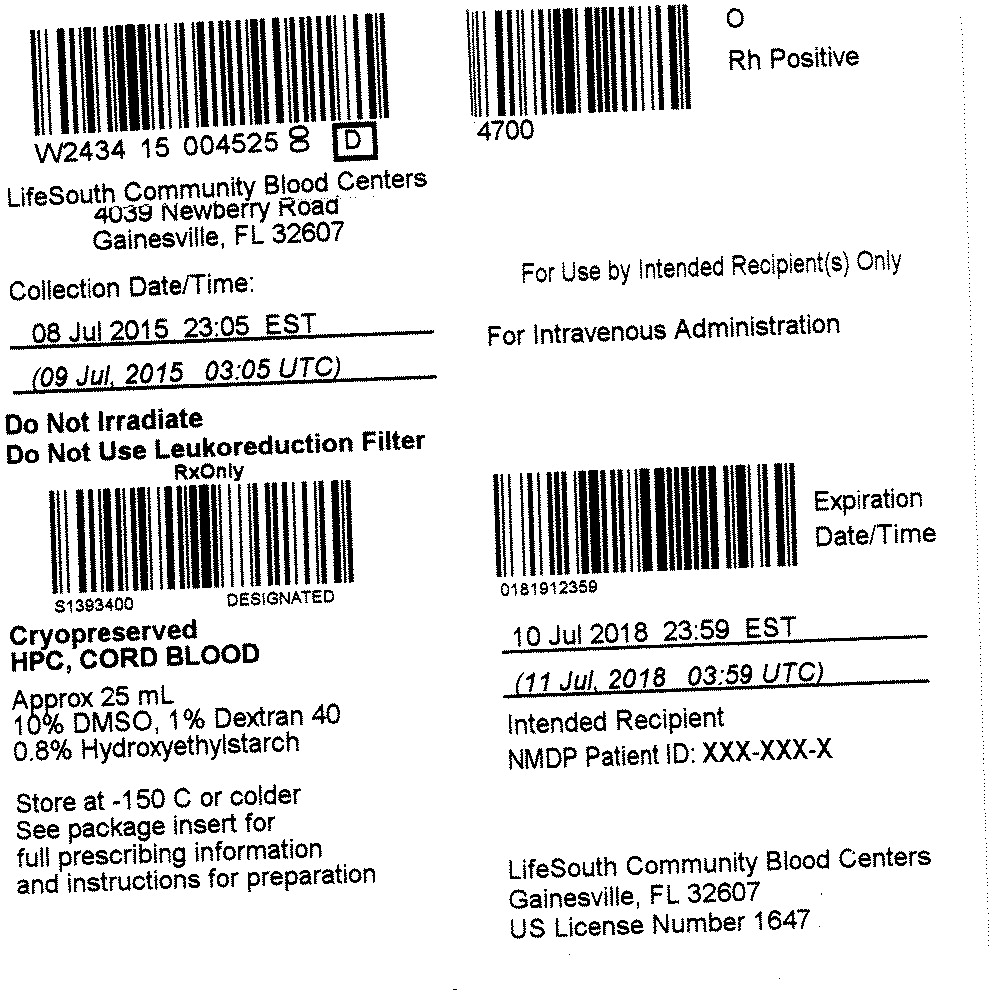 DRUG LABEL: CORDCYTE
NDC: W2434-S1393 | Form: INJECTION, SUSPENSION
Manufacturer: LifeSouth Community Blood Centers, Inc.
Category: other | Type: LICENSED MINIMALLY MANIPULATED CELLS LABEL
Date: 20151220

ACTIVE INGREDIENTS: human cord blood hematopoietic progenitor cell 500000000 1/25 mL
INACTIVE INGREDIENTS: dimethyl sulfoxide; hetastarch; Dextran 40

HIGHLIGHTS OF PRESCRIBING INFORMATION

These highlights do not include all the information needed to use CORDCYTE safely and effectively. See full prescribing information for CORDCYTE.
CORDCYTE (HPC, Cord Blood)
Injectable Suspension for Intravenous Use
Initial U.S. Approval: 2013

RECENT MAJOR CHANGES

Boxed Warning | 5/2015
Contraindications (4) | 5/2015

WARNING: FATAL INFUSION REACTIONS, GRAFT VERSUS HOST DISEASE, ENGRAFTMENT SYNDROME AND GRAFT FAILURE

See full prescribing information for complete boxed warning.

- Fatal infusion reactions: Monitor patients during infusion and discontinue for severe reactions. (5.1, 5.2).
- Graft-vs.-host disease (GVHD): GVHD may be fatal. Administration of immunosuppressive therapy may decrease the risk of GVHD (5.3).
- Engraftment syndrome: Engraftment syndrome may be fatal. Treat engraftment syndrome promptly with corticosteroids (5.4).
- Graft failure: Graft failure may be fatal. Monitor patients for laboratory evidence of hematopoietic recovery (5.5).

1 INDICATIONS AND USAGE

CORDCYTE, HPC, Cord Blood, is an allogeneic cord blood hematopoietic progenitor cell therapy indicated for use in unrelated donor hematopoietic progenitor cell transplantation procedures in conjunction with an appropriate preparative regimen for hematopoietic and immunologic reconstitution in patients with disorders affecting the hematopoietic system that are inherited, acquired, or result from myeloablative treatment (1).

The risk benefit assessment for an individual patient depends on the patient characteristics, including disease, stage, risk factors, and specific manifestations of the disease, on characteristics of the graft, and on other available treatments or types of hematopoietic progenitor cells (1).

2 DOSAGE AND ADMINISTRATION

- For intravenous use only
- Do not irradiate
- Unit selection and administration of CORDCYTE should be done under the direction of a physician experienced in hematopoietic progenitor cell transplantation (2).
- The recommended minimum dose is 2.5 x 10^7 nucleated cells/kg at cryopreservation (2.1).
- Do not administer CORDCYTE through the same tubing with other products except for normal saline (2.3).

3 DOSAGE FORMS AND STRENGTHS

Each unit contains a minimum of 5 x 10^8 total nucleated cells with at least 1.25 x 10^6 viable CD34+ cells at the time of cryopreservation. The exact pre-cryopreservation nucleated cell content of each unit is provided on the accompanying records (3).

4 CONTRAINDICATIONS

None.

5 WARNINGS AND PRECAUTIONS

- Hypersensitivity Reactions (5.1)
- Infusion Reactions (5.2)
- Graft-versus-Host Disease (5.3)
- Engraftment Syndrome (5.4)
- Graft Failure (5.5)
- Malignancies of Donor Origin (5.6)
- Transmission of Serious Infections (5.7)
- Transmission of Rare Genetic Diseases (5.8)

6 ADVERSE REACTIONS

Mortality, from all causes, at 100 days post-transplant was 25% (5, 6.1).

The most common infusion-related adverse reactions (≥ 5%) are hypertension, vomiting, nausea, bradycardia, and fever (6.1).

To report SUSPECTED ADVERSE REACTIONS, contact the quality department for LifeSouth Community Blood Centers at 1-888-795-2707 and FDA at 1-800-FDA-1088 or www.fda.gov/medwatch.

8 USE IN SPECIFIC POPULATIONS

Pregnancy: No animal or human data. Use only if clearly needed (8.1).

FULL PRESCRIBING INFORMATION

WARNING: FATAL INFUSION REACTIONS, GRAFT VERSUS HOST DISEASE, ENGRAFTMENT SYNDROME AND GRAFT FAILURE

Fatal infusion reactions: CORDCYTE administration can result in serious, including fatal, infusion reactions. Monitor patients and discontinue CORDCYTE infusion for severe reactions. [See Warnings and Precautions (5.1, 5.2)].

Graft-vs.-host disease (GVHD): GVHD is expected after administration of CORDCYTE, and may be fatal. Administration of immunosuppressive therapy may decrease the risk of GVHD. [See Warnings and Precautions (5.3)].

Engraftment syndrome: Engraftment syndrome may progress to multiorgan failure and death. Treat engraftment syndrome promptly with corticosteroids. [See Warnings and Precautions (5.4)].

Graft failure: Graft failure may be fatal. Monitor patients for laboratory evidence of hematopoietic recovery. Prior to choosing a specific unit of CORDCYTE, consider testing for HLA antibodies to identify patients who are alloimmunized. [See Warnings and Precautions (5.5)].

1 INDICATIONS AND USAGE

CORDCYTE, HPC (Hematopoietic Progenitor Cell), Cord Blood is an allogeneic cord blood hematopoietic progenitor cell therapy indicated for use in unrelated donor hematopoietic progenitor stem cell transplantation procedures in conjunction with an appropriate preparative regimen for hematopoietic and immunologic reconstitution in patients with disorders affecting the hematopoietic system that are inherited, acquired, or result from myeloablative treatment.

The risk benefit assessment for an individual patient depends on the patient characteristics, including disease, stage, risk factors, and specific manifestations of the disease, on characteristics of the graft, and on other available treatments or types of hematopoietic progenitor cells.

2 DOSAGE AND ADMINISTRATION

- For intravenous use only.
- Do not irradiate.

Unit selection and administration of CORDCYTE should be done under the direction of a physician experienced in hematopoietic progenitor cell transplantation.

2.1 Dosing

The recommended minimum dose is 2.5 x 10^7 nucleated cells/kg at cryopreservation. Multiple units may be required in order to achieve the appropriate dose.

Matching for at least 4 of 6 HLA-A antigens, HLA-B antigens, and HLA-DRB1 alleles is recommended. The HLA typing and nucleated cell content for each individual unit of CORDCYTE are documented in the accompanying records.

2.2 Preparation for Infusion

CORDCYTE should be prepared by a trained healthcare professional.

- Do not irradiate CORDCYTE.
- See the appended detailed instructions for preparation of CORDCYTE for infusion.
- Once prepared for infusion, CORDCYTE may be stored at room temperature (19-25ºC) or 4oC for up to 2 hours when DMSO is removed in a washing procedure [see Instructions for Preparation for Infusion]. No data are available for the stability of CORDCYTE if DMSO is not removed.
- The recommended limit on DMSO administration is 1 gram per kg body weight per day [see Warnings and Precautions (5.2) and Overdosage (10)].

2.3 Administration

CORDCYTE should be administered under the supervision of a qualified healthcare professional experienced in hematopoietic progenitor cell transplantation.

1. Confirm the identity of the patient for the specified unit of CORDCYTE prior to administration.
2. Confirm that emergency medications are available for use in the immediate area.
3. Ensure the patient is hydrated adequately.
4. Premedicate the patient 30 to 60 minutes before the administration of CORDCYTE. Premedication can include any or all of the following: antipyretics, histamine antagonists, and corticosteroids.
5. Inspect the product for any abnormalities such as unusual particulates and for breaches of container integrity prior to administration. Prior to infusion, discuss all such product irregularities with the laboratory issuing the product for infusion.
6. Administer CORDCYTE by intravenous infusion. Do not administer in the same tubing concurrently with products other than 0.9% Sodium Chloride, Injection (USP). CORDCYTE may be filtered through a 170 to 260 micron filter designed to remove clots. Do NOT use a filter designed to remove leukocytes.
7. For adults, begin infusion of CORDCYTE at 100 milliliters per hour and increase the rate as tolerated. For children, begin infusion of CORDCYTE at 1 milliliter per kg per hour and increase as tolerated. Reduce the infusion rate if the fluid load is not tolerated. Discontinue the infusion in the event of an allergic reaction or if the patient develops a moderate to severe infusion reaction [see Warnings and Precautions (5.2) and Adverse Reactions (6)].
8. Monitor the patient for adverse reactions during, and for at least six hours after, administration. Because CORDCYTE contains lysed red cells that may cause renal failure, careful monitoring of urine output is also recommended.

NOTE: If product is being prepared for a multi-unit infusion, infuse units independently. Should a reaction occur, appropriately manage the reaction before the second unit is thawed for infusion.

3 DOSAGE FORMS AND STRENGTHS

Each unit of CORDCYTE contains a minimum of 5 x 10^8 total nucleated cells with a minimum of 1.25 x 10^6 viable CD34+ cells, suspended in 10% dimethyl sulfoxide (DMSO) and 1% Dextran 40, at the time of cryopreservation.

The exact pre-cryopreservation nucleated cell content is provided in the accompanying records.

4 CONTRAINDICATIONS

None.

5 WARNINGS AND PRECAUTIONS

5.1 Hypersensitivity Reactions

Allergic reactions may occur with infusion of HPC, Cord Blood, including CORDCYTE. Reactions include bronchospasm, wheezing, angioedema, pruritus and hives [see Adverse Reactions (6)]. Serious hypersensitivity reactions, including anaphylaxis, also have been reported. These reactions may be due to dimethyl sulfoxide (DMSO), Dextran 40, hydroxyethylstarch, or a plasma component of CORDCYTE.

CORDCYTE may contain residual antibiotics if the cord blood donor was exposed to antibiotics in utero. Patients with a history of allergic reactions to antibiotics should be monitored for allergic reactions following CORDCYTE administration.

5.2 Infusion Reactions

Infusion reactions are expected to occur and include nausea, vomiting, fever, rigors or chills, flushing, dyspnea, hypoxemia, chest tightness, hypertension, tachycardia, bradycardia, dysgeusia, hematuria, and mild headache. Premedication with antipyretics, histamine antagonists, and corticosteroids may reduce the incidence and intensity of infusion reactions.

Severe reactions, including respiratory distress, severe bronchospasm, severe bradycardia with heart block or other arrhythmias, cardiac arrest, hypotension, hemolysis, elevated liver enzymes, renal compromise, encephalopathy, loss of consciousness, and seizure also may occur. Many of these reactions are related to the amount of DMSO administered. Minimizing the amount of DMSO administered may reduce the risk of such reactions, although idiosyncratic responses may occur even at DMSO doses thought to be tolerated. The actual amount of DMSO depends on the method of preparation of the product for infusion. Limiting the amount of DMSO infused to no more than 1 gram per kilogram per day is recommended [see Overdosage (10)].

Infusion reactions may begin within minutes of the start of infusion of CORDCYTE, although symptoms may continue to intensify and not peak for several hours after completion of the infusion. Monitor the patient closely during this period. When a reaction occurs, discontinue the infusion and institute supportive care as needed.

If infusing more than one unit of HPC, Cord Blood, on the same day, do not administer subsequent units until all signs and symptoms of infusion reactions from the prior unit have resolved.

5.3 Graft-versus-Host Disease

Acute and chronic graft-versus-host disease (GVHD) may occur in patients who have received CORDCYTE. Classic acute GVHD is manifested as fever, rash, elevated bilirubin and liver enzymes, and diarrhea. Patients transplanted with CORDCYTE also should receive immunosuppressive drugs to decrease the risk of GVHD. [See Adverse Reactions (6.1).]

5.4 Engraftment Syndrome

Engraftment syndrome is manifested as unexplained fever and rash in the peri-engraftment period. Patients with engraftment syndrome also may have unexplained weight gain, hypoxemia, and pulmonary infiltrates in the absence of fluid overload or cardiac disease. If untreated, engraftment syndrome may progress to multiorgan failure and death. Once engraftment syndrome is recognized, begin treatment with corticosteroids to ameliorate the symptoms. [See Adverse Reactions (6.1).]

5.5 Graft Failure

Primary graft failure, which may be fatal, is defined as failure to achieve an absolute neutrophil count greater than 500 per microliter blood by Day 42 after transplantation. Immunologic rejection is the primary cause of graft failure. Patients should be monitored for laboratory evidence of hematopoietic recovery. Consider testing for HLA antibodies in order to identify patients who are alloimmunized prior to transplantation and to assist with choosing a unit with a suitable HLA type for the individual patient. [See Adverse Reactions (6.1).]

5.6 Malignancies of Donor Origin

Patients who have undergone HPC, Cord Blood transplantation may develop post-transplant lymphoproliferative disorder (PTLD), manifested as a lymphoma-like disease favoring non-nodal sites. PTLD is usually fatal if not treated.

The incidence of PTLD appears to be higher in patients who have received antithymocyte globulin. The etiology is thought to be donor lymphoid cells transformed by Epstein-Barr virus (EBV). Serial monitoring of blood for EBV DNA may be warranted in high-risk groups.

Leukemia of donor origin also has been reported in HPC, Cord Blood recipients. The natural history is presumed to be the same as that for de novo leukemia.

5.7 Transmission of Serious Infections

Transmission of infectious disease may occur because CORDCYTE is derived from human blood. Disease may be caused by known or unknown infectious agents. Donors are screened for increased risk of infection with human immunodeficiency virus (HIV), human T-cell lymphotropic virus (HTLV), hepatitis B virus (HBV), hepatitis C virus (HCV), T. pallidum, T. cruzi, West Nile Virus (WNV), transmissible spongiform encephalopathy (TSE) agents, and vaccinia. Donors are also screened for clinical evidence of sepsis, and communicable disease risks associated with xenotransplantation. Maternal blood samples are tested for HIV types 1 and 2, HTLV types I and II, HBV, HCV, T. pallidum, WNV, and T. cruzi. CORDCYTE is tested for sterility. There may be an effect on the reliability of the sterility test results if the cord blood donor was exposed to antibiotics in utero. These measures do not totally eliminate the risk of transmitting these or other transmissible infectious diseases and disease agents. Report the occurrence of a suspected transmitted infection to the quality department of LifeSouth Community Blood Centers at 1-888-795-2707.

Testing is also performed for evidence of donor infection due to cytomegalovirus (CMV). Test results may be found in the accompanying records.

5.8 Transmission of Rare Genetic Diseases

CORDCYTE may transmit rare genetic diseases involving the hematopoietic system for which donor screening and/or testing has not been performed [see Adverse Reactions (6.1)]. Cord blood donors have been screened by family history to exclude inherited disorders of the blood and marrow. CORDCYTE has been tested to exclude donors with sickle cell anemia, and anemias due to abnormalities in hemoglobins C, D, and E. Because of the age of the donor at the time CORDCYTE collection takes place, the ability to exclude rare genetic diseases is severely limited.

6 ADVERSE REACTIONS

Day-100 mortality from all causes was 25%.

The most common infusion-related adverse reactions (≥ 5%) are hypertension, vomiting, nausea, bradycardia, and fever.

6.1 Clinical Trials Experience

Because clinical trials are conducted under widely varying conditions, adverse reaction rates observed in the clinical trials of a drug cannot be directly compared to rates in the clinical trials of another drug and may not reflect the rates observed in practice.

The safety assessment of CORDCYTE is based primarily on review of the data submitted to the FDA dockets from various sources, the dataset for the COBLT Study, and published literature.

Infusion Reactions

The data described in Table 1 reflect exposure to 442 infusions of HPC, Cord Blood (from multiple cord blood banks) in patients treated using a total nucleated cell dose ≥ 2.5 x 10^7/kg on a single-arm prospective trial or expanded access use (COBLT Study). The population was 60% male and the median age was 5 years (range 0.05-68 years), and included patients treated for hematologic malignancies, inherited metabolic disorders, primary immunodeficiencies, and bone marrow failure. Preparative regimens and graft-vs.-host disease prophylaxis were not standardized. The most common infusion reactions were hypertension, vomiting, nausea, and sinus bradycardia. Hypertension and any grades 3-4 infusion-related reactions occurred more frequently in patients receiving HPC, Cord Blood in volumes > 150 milliliters and in pediatric patients. The rate of serious adverse cardiopulmonary reactions was 0.8%.

Table 1: Incidence of Infusion-Related Adverse Reactions Occurring in ≥ 1% of Infusions (COBLT Study)
 | Any grade | Grade 3-4
Any reaction | 65.4% | 27.6%
Hypertension | 48.0% | 21.3%
Vomiting | 14.5% | 0.2%
Nausea | 12.7% | 5.7%
Sinus bradycardia | 10.4% | 0
Fever | 5.2% | 0.2%
Sinus tachycardia | 4.5% | 0.2%
Allergy | 3.4% | 0.2%
Hypotension | 2.5% | 0
Hemoglobinuria | 2.1% | 0
Hypoxia | 2.0% | 2.0%

No information on the types and rates of infusion reactions were reported with CORDCYTE.

Other Adverse Reactions

For other adverse reactions, the raw clinical data from the dockets were pooled for 1299 (120 adult and 1179 pediatric) patients transplanted with HPC, Cord Blood (from multiple cord blood banks) with total nucleated cell dose ≥ 2.5 x 10^7/kg. Of these, 66% (n=862) underwent transplantation as treatment for hematologic malignancy. The preparative regimens and graft-vs.-host disease prophylaxis varied. The median total nucleated cell dose was 6.4 x 10^7/kg (range, 2.5-73.8 x 10^7/kg). For these patients, Day-100 mortality from all causes was 25%. Primary graft failure occurred in 16%; 42% developed grades 2-4 acute graft-vs.-host disease; and 19% developed grades 3-4 acute graft-vs.-host disease.

Data from published literature and from observational registries, institutional databases, and cord blood bank reviews reported to the dockets for HPC, Cord Blood (from multiple cord blood banks) revealed nine cases of donor cell leukemia, one case of transmission of infection, and one report of transplantation from a donor with an inheritable genetic disorder. The data are not sufficient to support reliable estimates of the incidences of these events.

In the COBLT Study, 15% of the patients developed engraftment syndrome.

8 USE IN SPECIFIC POPULATIONS

8.1 Pregnancy

Pregnancy Category C. Animal reproduction studies have not been conducted with CORDCYTE. It is also not known whether CORDCYTE can cause fetal harm when administered to a pregnant woman or can affect reproduction capacity. There are no adequate and well-controlled studies in pregnant women. CORDCYTE should be used during pregnancy only if the potential benefit justifies the potential risk to the fetus.

8.4 Pediatric Use

HPC, Cord Blood has been used in pediatric patients with disorders affecting the hematopoietic system that are inherited, acquired, or resulted from myeloablative treatment [see Dosage and Administration (2), Adverse Reactions (6), and Clinical Studies (14)].

8.5 Geriatric Use

Clinical studies of HPC, Cord Blood (from multiple cord blood banks) did not include sufficient numbers of subjects aged 65 years and over to determine whether they respond differently than younger subjects. In general, administration of CORDCYTE to patients over age 65 years should be cautious, reflecting their greater frequency of decreased hepatic, renal, or cardiac function, and of concomitant disease or other drug therapy.

8.6 Renal Disease

CORDCYTE contains Dextran 40 which is eliminated by the kidneys. The safety of CORDCYTE has not been established in patients with renal insufficiency or renal failure.

10 OVERDOSAGE

10.1 Human Overdosage Experience

There has been no experience with overdosage of HPC, Cord Blood in human clinical trials. Single doses of LifeSouth CORDCYTE up to 71 x 10^7 TNC/kg have been administered. HPC, Cord Blood prepared for infusion may contain dimethyl sulfoxide (DMSO). The maximum tolerated dose of DMSO has not been established, but it is customary not to exceed a DMSO dose of 1 gm/kg/day when given intravenously. Several cases of altered mental status and coma have been reported with higher doses of DMSO.

10.2 Management of Overdose

For DMSO overdosage, general supportive care is indicated. The role of other interventions to treat DMSO overdosage has not been established.

11 DESCRIPTION

CORDCYTE consists of hematopoietic progenitor cells, monocytes, lymphocytes, and granulocytes from human cord blood for intravenous infusion. Blood recovered from umbilical cord and placenta is volume reduced and partially depleted of red blood cells and plasma.

The active ingredient is hematopoietic progenitor cells which express the cell surface marker CD34. The potency of cord blood is determined by measuring the numbers of total nucleated cells (TNC) and CD34+ cells, and cell viability. Each unit of CORDCYTE contains a minimum of 5 x 10^8 total nucleated cells with at least 1.25 x 10^6 viable CD34+ cells at the time of cryopreservation. The cellular composition of CORDCYTE depends on the composition of cells in the blood recovered from the umbilical cord and placenta of the donor. The actual nucleated cell count, the CD34+ cell count, the ABO group, and the HLA typing are listed in the accompanying records sent with each individual unit.

CORDCYTE has the following inactive ingredients: dimethyl sulfoxide (DMSO), Dextran 40, and hydroxyethylstarch. When prepared for infusion according to instructions, the infusate contains the following inactive ingredients: Dextran 40, human serum albumin, residual DMSO, and residual hydroxyethylstarch.

12 CLINICAL PHARMACOLOGY

12.1 Mechanism of Action

Hematopoietic stem/progenitor cells from HPC, Cord Blood migrate to the bone marrow where they divide and mature. The mature cells are released into the bloodstream, where some circulate and others migrate to tissue sites, partially or fully restoring blood counts and function, including immune function, of blood-borne cells of marrow origin. [See Clinical Studies (14).]

In patients with enzymatic abnormalities due to certain severe types of storage disorders, mature leukocytes resulting from HPC, Cord Blood transplantation may synthesize enzymes that may be able to circulate and improve cellular functions of some native tissues. However, the precise mechanism of action is unknown.

14 CLINICAL STUDIES

The effectiveness of CORDCYTE, as defined by hematopoietic reconstitution, was demonstrated in one single-arm prospective study (COBLT Study), and in retrospective reviews of data from an observational database for CORDCYTE and data in the dockets and public information. Of the 1299 patients in the dockets and public data, 66% (n=862) underwent transplantation as treatment for hematologic malignancy. Results for patients who received a total nucleated cell dose ≥ 2.5 x 10^7/kg are shown in Table 2. Neutrophil recovery is defined as the time from transplantation to an absolute neutrophil count more than 500 per microliter. Platelet recovery is the time to a platelet count more than 20,000 per microliter. Erythrocyte recovery is the time to a reticulocyte count greater than 30,000 per microliter. The total nucleated cell dose and degree of HLA match were inversely associated with the time to neutrophil recovery in the docket data.

Table 2: Hematopoietic Recovery for Patients Transplanted with HPC, Cord Blood, Total Nucleated Cell (TNC) Dose ≥ 2.5 x 10^7/kg
Data Source | COBLT Study* | Docket* and Public Data* | CORDCYTE
Design | Single-arm prospective | Retrospective | Retrospective
Number of patients | 324 | 1299 | 22
Median age (years) (range) | 4.6 (0.07 – 52.2) | 7.0 (<1 – 65.7) | 8 (0.6 – 61.8)
Gender | 59% male 41% female | 57% male 43% female | 59% male 41% female
Median TNC Dose (x 10^7/kg) (range) | 6.7 (2.6 – 38.8) | 6.4 (2.5 – 73.8) | 5.1 (2.8 – 70.6)
Neutrophil Recovery at Day 42 (95% CI) | 76% (71% – 81%) | 77% (75% – 79%) | 91% (71% - 98%)
Platelet Recovery at Day 100 of 20,000/microliter (95% CI) | 57% (51% – 63%) | - | 95% (79% - 99%)
Platelet Recovery at Day 100 of 50,000/microliter (95% CI) | 46% (39% – 51%) | 45% (42% – 48%) | 95% (79% - 99%)
Erythrocyte Recovery at Day 100 (95% CI) | 65% (58% – 71%) | - | -
Median time to Neutrophil Recovery | 27 days | 25 days | 22 days
Median time to Platelet Recovery of 20,000/microliter | 90 days | - | 44 days
Median time to Platelet Recovery of 50,000/microliter | 113 days | 122 days | 70 days
Median time to Erythrocyte Recovery | 64 days | - | -
* HPC, Cord Blood (from multiple cord blood banks)

16 HOW SUPPLIED/STORAGE AND HANDLING

CORDCYTE is supplied as a cryopreserved cell suspension in a sealed bag containing a minimum of 5 x 10^8 total nucleated cells with a minimum of 1.25 x 10^6 viable CD34+ cells in a volume of 25 milliliters (ISBT 128 Product Code S1393, ISBT 128 Facility Identifier Number W2434). The exact pre-cryopreservation nucleated cell content is provided in the accompanying records.

Store CORDCYTE at or below -150°C until ready for thawing and preparation.

17 PATIENT COUNSELING INFORMATION

Discuss the following with patients receiving CORDCYTE:

- Report immediately any signs and symptoms of acute infusion reactions, such as fever, chills, fatigue, breathing problems, dizziness, nausea, vomiting, headache, or muscle aches.
- Report immediately any signs or symptoms suggestive of graft-vs.-host disease, including rash, diarrhea, or yellowing of the eyes.

INSTRUCTIONS FOR PREPARATION FOR INFUSION

The CORDCYTE unit is stored continuously inside a steel canister in liquid nitrogen at temperatures ≤ -150° C. For shipment, the canister is placed inside a container specifically designed to keep the temperature at or below -150° C (dry shipper). It is recommended to keep the canister inside the dry shipper for short-term storage (up to 48 hours) or transfer it into a liquid nitrogen (LN2)-cooled storage device at the Transplant Center for storage greater than 48 hours.

1. MATERIALS
  Equipment:
  - Refrigerated centrifuge
  - Plasma extractor/expressor
  - Biological safety cabinet
  - Scale
  - Tube sealer compatible with polyvinyl chloride plastic
  - Water bath
  - Canister-opening tool (supplied by LifeSouth Community Blood Centers)
  - LN2 storage freezer at -150° C or colder
  - Sterile docker
  - Automated cell counter and/or microscope and cell count chamber for cell count and viability determination (optional)
  Personal Protective Equipment:
  - Gloves (sterile preferred)
  - Protective cryogloves
  - Safety goggles or face shield
  - Lab coat
  Reagents:
  - 10% Dextran 40 in Sodium Chloride Injection, USP
  - 5% Albumin (Human), USP
  Supplies:
  - Sterile disposable syringes - (2) 30-mL, (8) 60-mL
  - 18-gauge injection needles
  - Hemostat
  - Small plastic zip-lock bags (sterile preferred)
  - Alcohol prep pads
  - (3) sampling site couplers
  - (4) 300-mL transfer bags
  - Sterile pipettes
  - Sterile sampling cups
  - Bacterial culture bottles (aerobic and anaerobic) or other supplies for conducting sterility testing
  - Tubes for cell counts, progenitor assays (optional)
  Forms:
  - Receipt of Cord Blood Unit form
  - Umbilical Cord Blood Cryopreserved Transfer Report form
2. PRODUCT IDENTITY VERIFICATION
  1. Apply personal protective equipment.
  2. Open the dry shipper lid upon receipt using scissors to remove the tie-tag from the outside of the shipper.
  3. Verify that the National Marrow Donor Program (NMDP) number on the tie-tag matches the NMDP number on the Umbilical Cord Blood Cryopreserved Unit Transfer Report. If the NMDP numbers do not match, contact LifeSouth Community Blood Centers (LifeSouth) at 1-888-795-2707.
  4. Remove the canister from the dry shipper and the canister-opening tool from the shipment documentation packet (see Figure 1).
    Figure 1:
  5. Compare product bar code information on bar-coded label on the side of the canister (see Figure 1) with the product identification (ID) information included in the packaging. Verify this information as soon as the shipment arrives and before administering the CORDCYTE unit. If the bar-coded label is not found on the outside of the canister, the product bar code information can be found on the frozen cord blood unit enclosed in the canister.
  6. Using protective cryogloves and the canister-opening tool, open the canister at top and bottom using the following steps:
    1. Avoid damaging the frozen cord blood bag.
    2. Align the canister opening tool with the slot in the bottom of the canister (see Figure 2).
    3. Turn the canister opening tool clockwise to open the bottom of the canister (see Figure 3).
      Figure 2:
      Figure 3:
      Figure 4:
    4. Locate the opening at the top of the canister and use the tool in a counterclockwise motion to open the top of the canister (see Figure 4).
    5. Open the canister hinges so the CORDCYTE unit can be removed (see Figure 5).
    Figure 5:
  7. Once the canister is open, compare the product bar code information with your records.
  8. Close canister after verification is complete. Using protective cryogloves, return the canister to the dry shipper for short term storage (up to 48 hours) or to LN2-cooled storage device for storage greater than 48 hours.
  9. Once records are all verified, indicate acceptance by initial and date on the indicated space on the Receipt of Cord Blood Unit and Umbilical Cord Blood Cryopreserved Transfer Report forms.
    For Incorrect Information:
    1. If any information is incorrect or cannot be verified, close the canister and return the frozen unit to the dry shipper for short term storage (up to 48 hours) or into a LN2-cooled storage device for storage greater than 48 hours.
    2. Report the discrepancy immediately to LifeSouth at 1-888-795-2707 and to the transplant physician.
    3. Perform a thorough investigation, keeping the CORDCYTE unit frozen at or below -150° C until all discrepancies are resolved.
    4. Once records are all verified, indicate acceptance by initial and date on the indicated space on the Receipt of Cord Blood Unit and Umbilical Cord Blood Cryopreserved Transfer Report forms.
3. PREPARATION
  1. Prepare Thawing Solution
    1. Label a 300-mL transfer bag "Thaw/Wash Solution" (see Figure 6 below).
    2. Clamp the “Thaw/Wash Solution” bag with a hemostat to prevent leaking.
    3. Refrigerate the 10% Dextran 40 in Sodium Chloride Injection, USP and the 5% Albumin (Human), USP at 2-6ºC.
    4. Complete the following steps inside a biological safety cabinet:
      1. Add 72.5 mL of refrigerated 10% Dextran 40 in Sodium Chloride Injection, USP to the 300-mL transfer bag labeled Thaw/Wash Solution using two 60-mL sterile syringes.
      2. Add 72.5 mL of refrigerated 5% Albumin (Human), USP to the same 300-mL transfer bag labeled Thaw/Wash Solution using two 60-mL syringes.
      3. Mix by inverting the bag at least 10 times.
      4. Label a 60-mL sterile syringe "Resuspension Solution"; fill with 50 mL of the solution from transfer bag labeled Thaw/Wash Solution (1:1 ratio of 10% Dextran 40 in Sodium Chloride Injection, USP / 5% Albumin (Human), USP) for final end-product re-suspension. Refrigerate until ready for use.
      5. Label two 60-mL sterile syringes and two 30-mL sterile syringes as "Thaw/Wash Solution."
      6. For the two 60-mL syringes draw 20 mL of thaw/wash solution into each syringe; refrigerate until ready for use.
        1. For the two 30-mL syringes draw 5 mL of thaw/wash solution into each syringe; refrigerate until ready for use.
        2. Using a sterile docker, connect two 300-mL transfer bags into a transfer set (see Figure 6 below).
      7. Label one transfer bag with the CORDCYTE unit Donation Identification Number (DIN) and "Thaw/Wash Solution."
        1. Label the second transfer bag with the CORDCYTE unit DIN and "Expressed Solution."
        2. Insert a sampling site coupler into the port closest to the tubing on the DIN and Thaw/Wash Solution labeled transfer bag (see Figure 6).
      8. Attach a hemostat to the tubing approximately one inch above the sampling site coupler on the DIN and Thaw/Wash Solution transfer bag (see Figure 6).
    Figure 6: Transfer Set Diagram
  2. Thaw CORDCYTE Unit
    Schedule the infusion time of the transplant with the transplant team in advance of the procedure. Re-confirm on the day of infusion with the transplant team so that the start time for the thawing procedure can be adjusted to have the unit ready for infusion at a time the patient can receive the infusion.
    If canister is stored in LN2, wear protective cryogloves, lift canister containing the CORDCYTE unit from the liquid phase of the LN2 container, and rest canister in the vapor phase within the container for five to ten minutes before proceeding.
    Note: Carefully check the identity of the unit to be thawed.
    1. Open canister with the canister opening tool (refer to section II PRODUCT IDENTITY VERIFICATION). Avoid damage to the plastic bag containing the frozen CORDCYTE unit. Carefully examine the plastic bag for breaks or cracks.
    2. Remove the CORDCYTE unit bag from the canister.
    3. Place the CORDCYTE unit bag into a clean plastic zip-lock bag. Let the air out, and close it tightly. Use a sterile plastic zip-lock bag if available.
    4. Place the plastic zip-lock bag containing the frozen cord blood unit into a warm water bath at a temperature of 37° C +/- 1° C. Gently and carefully agitate the bag in the water bath to accelerate thawing and resuspension of the cells. Use your fingers to massage the bag to ensure equitable distribution of heat (see Figure 7).
      Figure 7:
    5. Watch closely for any cracks or breaks, as shown by red cells leaking from the cord blood bag into the plastic zip-lock bag.
    6. If any leakage is seen, keep the leakage site upright to prevent further leaking while continuing to gently agitate the bag until the product is slushy. (See section V EMERGENCY RECOVERY PROCEDURE IN THE EVENT OF A CONTAINER FAILURE for procedures for emergency recovery of the thawed cord blood cells).
    7. If no leakage is seen, remove the plastic zip-lock bag from water bath. Dry the outside of the bag, disinfect it with alcohol, and place it inside a biological safety cabinet.
  3. Transfer the Thawed CORDCYTE Unit to Transfer Set
    Complete the following steps inside a biological safety cabinet:
    1. Obtain pre-labeled transfer set (see section IIIA, step 4vi).
    2. Obtain CORDCYTE unit; clean both sealed ports with alcohol.
    3. Obtain scissors; disinfect port covers and cut off top of port to create an opening for insertion of sampling site coupler.
    4. Disinfect cut port-cover surfaces with alcohol and attach one sample site coupler to each port.
    5. Obtain one of the prepared 30-mL syringes containing 5 mL of thaw/wash solution (see section IIIA, step 4v).
    6. Connect the 30-mL syringe into the 5-mL cord blood compartment port; slowly dispense thaw/wash solution into this compartment.
    7. Slowly pull back and push in the syringe plunger to mix the cord blood and thaw/wash solution; repeat three to four times. After the last one, draw all the fluid from the compartment into the syringe.
    8. Disperse all the fluid in the syringe obtained in step 7 into the labeled DIN and Thaw/Wash Solution bag.
    9. Repeat steps 5 through 8 with the second prepared 30-mL syringe containing 5 mL of thaw/wash solution to wash any remaining CORDCYTE from the 5-mL compartment. The DIN and Thaw/Wash Solution Bag should contain 15 mL of CORDCYTE and solution.
    10. Obtain one of the prepared 60-mL syringes containing 20 mL of thaw/wash solution (see section IIIA, step 4v).
    11. Connect the 60-mL syringe into the larger 20-mL cord blood compartment port; slowly dispense the thaw/wash solution into this compartment.
    12. Slowly pull back and push in the syringe plunger to mix the cord blood and thaw/wash solution; repeat three to four times. After the last one, draw all the fluid from the compartment into the syringe.
    13. Disperse all the fluid in the syringe obtained in step 12 into the labeled DIN and Thaw/Wash Solution bag.
    14. Repeat steps 10 through 14 using the second prepared 60-mL syringe containing 20 mL of thaw/wash solution to wash the remaining contents from the 20-mL compartment. The DIN and Thaw/Wash Solution bag should contain 75 mL of CORDCYTE and solution.
    15. Allow five minutes for the mixture to equilibrate.
    16. Draw any remaining thaw/wash solution from the Thaw/Wash Solution transfer bag into a 60-mL syringe and add solution into the DIN and Thaw/Wash Solution transfer bag. The DIN and Thaw/Wash Solution bag should contain approximately 120 mL of CORDCYTE and solution.
    17. Mix the DIN and Thaw/Wash Solution transfer bag well by inverting the transfer bag 180° 10 to 15 times.
    18. Discard the empty Thaw/Wash Solution bag.
  4. Wash the Thawed CORDCYTE Unit
    1. Place the DIN and Thaw/Wash Solution transfer bag containing the hemostat, sampling site coupler, and DIN and Expressed Solution transfer bag into refrigerated centrifuge in upright position. Do not allow bags to crease. Inserts may be used to achieve upright position and to prevent damage as a result of centrifugation with a sampling site coupler.
    2. Balance the centrifuge before beginning centrifugation cycle.
    3. Centrifuge at 400 g for 20 minutes at 10°C.
    4. After centrifugation, look for clear separation of red blood cell (RBC) pellet.
    5. Place transfer bag labeled DIN and Thaw/Wash Solution into a plasma extractor (see Figure 8) and allow the supernatant to flow into the transfer bag labeled DIN and Expressed Solution by removing the hemostat from the tubing. Do not disturb the cells. If cells transfer, restore everything back into the primary transfer bag, re-centrifuge, and repeat extraction procedure.
      Figure 8:
    6. Allow all supernatant to leave bag but do not allow the RBC pellet to escape (see Figure 9). Hemostat the tubing after expressing to close tubing on the DIN and Thaw/Wash Solution transfer bag. Seal tubing with heat sealer on DIN and Thaw/Wash Solution transfer bag where the tubing begins. Make two seals; cut in between the two seals. Discard the line and DIN and Express Solution transfer bag.
      Figure 9:
    7. Obtain the prepared 60-mL “Resuspension Solution” syringe containing 50 mL thaw/wash solution (see section IIIA, step 4iv). Slowly add 50 mL of thaw/wash solution to the DIN and Thaw/Wash Solution transfer bag.
    8. Obtain an unlabeled 300 mL transfer bag. Seal the tubing of the transfer bag approximately one inch above the introduction of the tubing into the bag. Remove the excess tubing. Weigh the bag to obtain a tare weight of the transfer bag.
    9. Weigh the DIN and Thaw/Wash Solution bag. Calculate volume based on weight of bag minus tare weight obtained in step 8.
    10. Complete sampling for CFU, TNC, CD34+, viability, and ABO/Rh and HLA, if necessary.
    11. Label DIN and Thaw/Wash Solution transfer bag with the expiration time and the time of completion of washing. The recommended expiration time is 2 hours after the completion of wash until infusion, if stored at room temperature (19-25ºC) or 4 ºC.
    12. Notify the Transplant Center that the CORDCYTE unit is thawed, washed, and available for infusion.
4. ADMINISTRATIVE REQUIREMENTS
  1. Prepare a written summary of the procedure, including:
    1. CORDCYTE ID number
    2. Date of receipt of CORDCYTE unit
    3. Liquid nitrogen storage temperature
    4. Date of thaw, including whether and at what stage leaks or cracks occurred
    5. Date and time CORDCYTE unit removed from liquid nitrogen storage
    6. Volume of final product
    7. TNC (Total nucleated cell) count, CD34+ count
    8. Viability of recovered cells (TNC or CD34+) plus name of method used
    9. Results of bacterial and fungal cultures
  2. Make a copy of the report for your records.
  3. Fax a copy of the report to LifeSouth at 352-224-1650.
  4. Return the dry shipper to LifeSouth. The return address is:
    LifeSouth Community Blood Centers, Inc.
      LifeCord Cord Blood Bank
      4039 Newberry Road
      Gainesville, FL 32607
    Phone: 888-795-2707 x 41738
      Fax: 352-224-1650
5. EMERGENCY RECOVERY PROCEDURE IN THE EVENT OF A CONTAINER FAILURE
  1. Handle the frozen cord blood bag with extreme care at every step including opening the metal containers, inspecting, thawing and/or washing.
  2. Use standard procedures and competent personnel to perform post-thaw sampling and/or bag rescue.
  3. Perform all steps on lab benches, under biological safety cabinet, or another surface to prevent inadvertent drop of the frozen unit.
  4. To facilitate thawing, gradually remove the CORDCYTE unit from the liquid phase of the LN2 storage area, suspending in the vapor phase for at least five minutes prior to bringing the container to room temperature.
  5. Put the frozen bag inside a zip-lock bag prior to initiating the thaw to facilitate salvage of the product and to reduce the possibility of contamination.
  6. If the CORDCYTE unit is seen to be cracked when removed from the LN2 storage container, or if cracks or leaks occur during thawing, immediately notify LifeSouth at 1-888-795-2707. Notify the transplant physician/team and the laboratory director as soon as possible.
  7. The transplant physician or team will determine whether to use or discard the CORDCYTE product and whether any additional units should be requested.
  8. If the transplant physician or team decides that the product in the leaking unit could be used, the CORDCYTE unit may be recovered as follows:
    1. Obtain sterile sampling cups and sterile pipettes.
    2. Open a sterile sampling cup and set cup in working space to receive contents of zip-lock bag.
    3. If any contents remain in the broken CORDCYTE unit bag, remove the contents from the bag using the syringes prepared in section IIIA.
    4. Wash all contents out of the CORDCYTE bag and place contents in the DIN and Thaw/Wash Solution labeled transfer bag.
    5. Using a sterile syringe, transfer 20 mL from the Thaw/Wash Solution bag into a sterile sample cup.
    6. Using a sterile pipette, obtain 3 mL of thaw/wash solution from the sample cup and inject into the zip-lock bag containing the remaining CORDCYTE unit contents that leaked when thawing.
    7. Using a different sterile pipette, remove CORDCYTE and thaw/wash solution from the zip-lock bag and place in a sterile sample cup.
    8. Repeat steps f through g until all remaining CORDCYTE is transferred to the sterile sample cup.
    9. Using a sterile 20-mL syringe, draw the contents from the sterile sampling cup into the syringe. Inject the solution into the transfer bag labeled DIN and Thaw/Wash Solution.
    10. Repeat until all of the contents from the sample cup is transferred into the DIN and Thaw/Wash Solution transfer bag.
    11. After all contents have been transferred from the sample cup and are contained in the DIN and Thaw/Wash Solution transfer bag, mix well by inverting 180° 10 to 15 times.
    12. Continue with Section D Wash the Thawed CORDCYTE Unit.

Distributed by:

LifeSouth Community Blood Centers, Inc.
LifeCord Cord Blood Bank
4039 Newberry Road
Gainesville, FL 32607
License No. 1647

Principal Display Panel - Bag Label

Product:

S1393V00

LifeSouth
Community
Blood Center
Gainsville
FL
32607

CRYOPRESERVED

HPC, CORD BLOOD

Store at - 150 C or colder

Principal Display Panel - Canister Label

Principal Display Panel - Bag Label

LifeSouth Community Blood Centers

4039 Newberry Road

Gainesville, FL 32607

Collection Date/Time:

05 Jul 2015 23:05 EST

(09 Jul, 2015 03:05 UTC)

O

Rh Positive

For Use by Intended Recipient(s) Only

For Intravenous Administration

Do Not Irradiate

Do Not Use Leukoreduction Filter

Rx Only

Cryopreserved

HPC, CORD BLOOD

Approx 25 mL

10% DMSO, 1% Dextran 40

0.8% Hydroxyethylstarch

Store at -150 C or colder

See package insert for
full prescribing information
and instructions for preparation

Expiration

Date/Time

10 Jul 2018 23:59 EST

(11 Jul, 2018 03:59 UTC)

Intended Recipient

NMDP Patient ID: XXX-XXX-X

LifeSouth Community Blood Centers

Gainesville, FL 32607

US License Number 1647